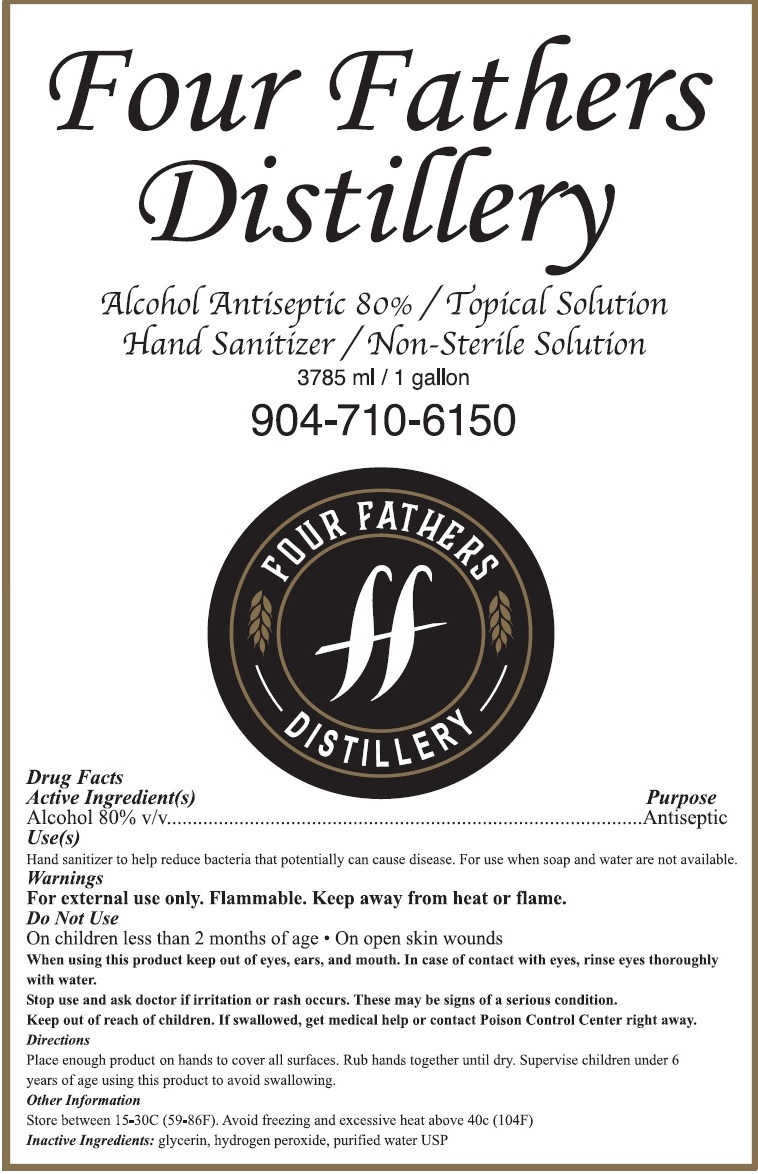 DRUG LABEL: Four Fathers Distillery
NDC: 78829-100 | Form: SOLUTION
Manufacturer: Four Fathers Distillery LLC
Category: otc | Type: HUMAN OTC DRUG LABEL
Date: 20201008

ACTIVE INGREDIENTS: ALCOHOL 80 mL/100 mL
INACTIVE INGREDIENTS: GLYCERIN; HYDROGEN PEROXIDE; WATER

Four Fathers Distillery Alcohol Antiseptic 80%

Active Ingredient(s)

Alcohol 80% v/v

Purpose

Antiseptic

Use(s)

Hand sanitizer to help reduce bacteria that potentially can cause disease. For use when soap and water are not available.

Warnings

For external use only. Flammable. Keep away from heat or flame.

Do Not Use

On children less than 2 months of age • On open skin wounds

When using this product keep out of ears, and mouth. In case of contact with eyes, rinse eyes thoroughly with water.

Stop use and ask a doctor if irritation or rash occurs. These may be signs of serious condition.

Keep out of reach of children.

If swallowed, get medical help or contact Poison Control Center right away.

Directions

Place enough product on hands to cover all surfaces. Rub hands together until dry. Supervise children under 6 years of age using this product to avoid swallowing.

Other Information

Store between 15-30C (59-86F). Avoid freezing and excessive heat above 40c(104F)

Inactive ingredients:

glycerin, hydrogen peroxide, purified water USP

Alcohol Antiseptic 80%/ Topical Solution

Hand Sanitizer/ Non-Sterile Solution

904-710-6150